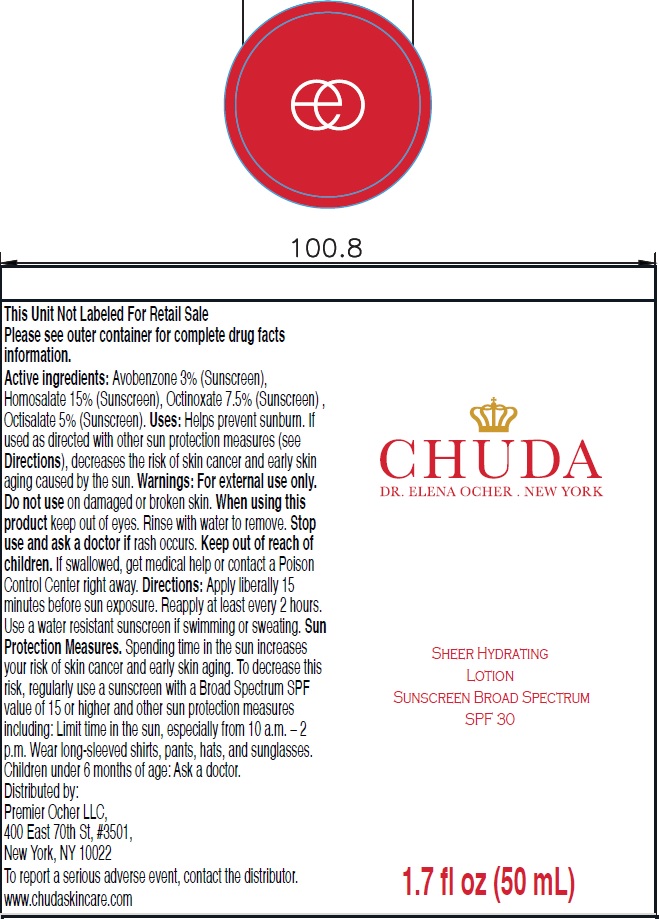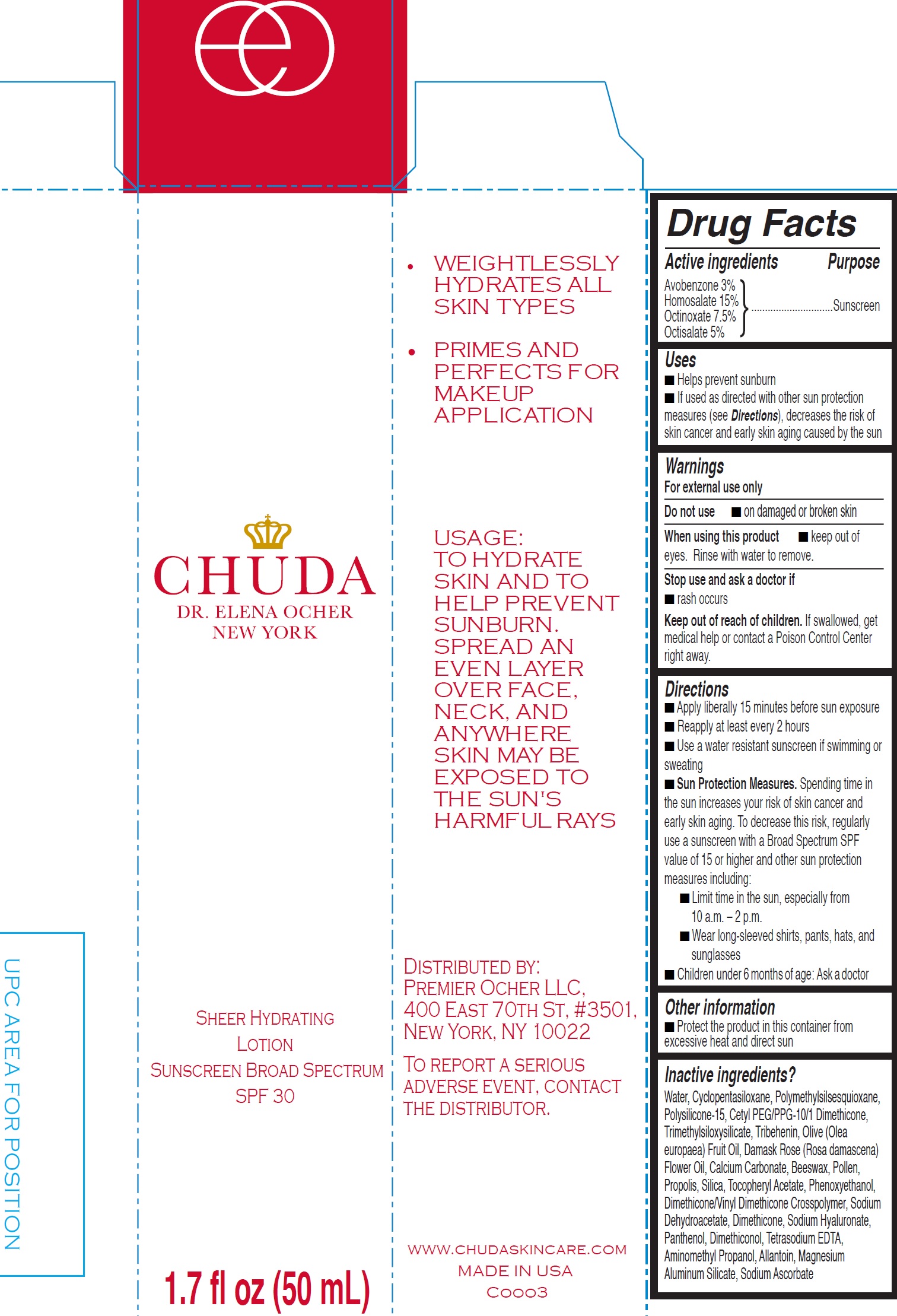 DRUG LABEL: CHUDA
NDC: 71784-000 | Form: CREAM
Manufacturer: Premier Ocher LLC
Category: otc | Type: HUMAN OTC DRUG LABEL
Date: 20260120

ACTIVE INGREDIENTS: AVOBENZONE 30 mg/1 mL; HOMOSALATE 150 mg/1 mL; OCTINOXATE 75 mg/1 mL; OCTISALATE 50 mg/1 mL
INACTIVE INGREDIENTS: WATER; CYCLOMETHICONE 5; POLYMETHYLSILSESQUIOXANE (4.5 MICRONS); POLYSILICONE-15; TRIBEHENIN; OLIVE OIL; ROSA X DAMASCENA FLOWERING TOP; CALCIUM CARBONATE; YELLOW WAX; POLLEN; PROPOLIS WAX; SILICON DIOXIDE; .ALPHA.-TOCOPHEROL ACETATE; PHENOXYETHANOL; SODIUM DEHYDROACETATE; DIMETHICONE; HYALURONATE SODIUM; PANTHENOL; EDETATE SODIUM; AMINOMETHYLPROPANOL; ALLANTOIN; MAGNESIUM ALUMINUM SILICATE; SODIUM ASCORBATE

Active ingredients

Avobenzone 3% Homosalate 15% Octinoxate 7.5%

Octisalate 5%

Purpose

Sunscreen

Uses

- Helps prevent sunburn
- If used as directed with other sun protection measures (see), decreases the risk of skin cancer and early skin aging caused by the sun Directions

Warnings

For external use only

Do not use

- on damaged or broken skin

When using this product

- keep out of eyes. Rinse with water to remove.

Stop use and ask a doctor if

rash occurs

Keep out of reach of children.

If swallowed, get medical help or contact a Poison Control Center right away.

Directions

- Apply liberally 15 minutes before sun exposure
- Reapply at least every 2 hours
- Use a water resistant sunscreen if swimming or sweating
- Spending time in the sun increases your risk of skin cancer and early skin aging. To decrease this risk, regularly use a sunscreen with a Broad Spectrum SPF value of 15 or higher and other sun protection measures including: Sun Protection Measures.
- Limit time in the sun, especially from 10 a.m. – 2 p.m.
- Wear long-sleeved shirts, pants, hats, and sunglasses
- Children under 6 months of age: Ask a doctor

Other information

Protect the product in this container from excessive heat and direct sun

Inactive ingredients?

Water, Cyclopentasiloxane, Polymethylsilsesquioxane, Polysilicone-15, Cetyl PEG/PPG-10/1 Dimethicone, Trimethylsiloxysilicate, Tribehenin, Olive (Olea europaea) Fruit Oil, Damask Rose (Rosa damascena) Flower Oil, Calcium Carbonate, Beeswax, Pollen, Propolis, Silica, Tocopheryl Acetate, Phenoxyethanol, Dimethicone/Vinyl Dimethicone Crosspolymer, Sodium Dehydroacetate, Dimethicone, Sodium Hyaluronate, Panthenol, Dimethiconol, Tetrasodium EDTA, Aminomethyl Propanol, Allantoin, Magnesium Aluminum Silicate, Sodium Ascorbate